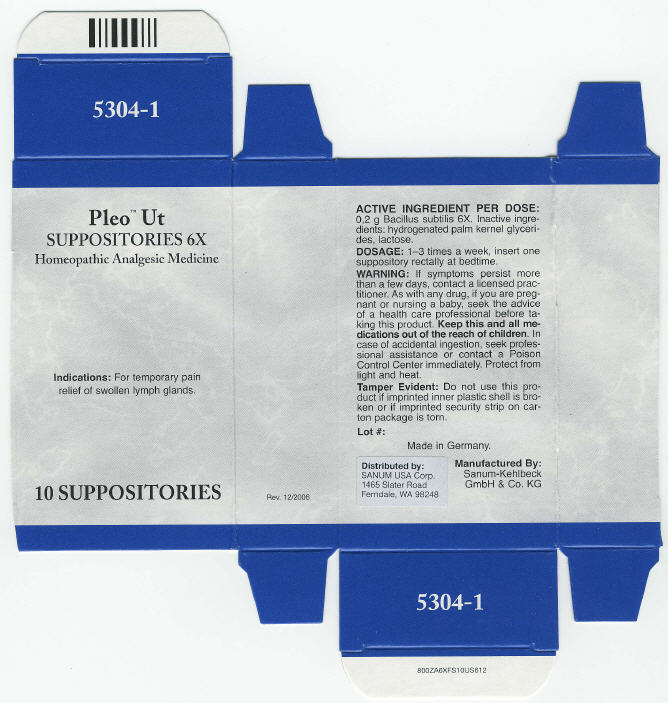 DRUG LABEL: Pleo Ut
NDC: 60681-5304 | Form: SUPPOSITORY
Manufacturer: Sanum Kehlbeck GmbH & Co. KG
Category: homeopathic | Type: HUMAN OTC DRUG LABEL
Date: 20091013

ACTIVE INGREDIENTS: bacillus subtilis 6 [HP_X]/1 1
INACTIVE INGREDIENTS: lactose

Pleo™ Ut
SUPPOSITORIES 6X

Homeopathic Analgesic Medicine

10 SUPPOSITORIES

Indications

For temporary pain relief of swollen lymph glands.

ACTIVE INGREDIENT PER DOSE

0.2 g Bacillus subtilis 6X.

Inactive ingredients

hydrogenated palm kernel glycerides, lactose.

DOSAGE

1–3 times a week, insert one suppository rectally at bedtime.

WARNING

If symptoms persist more than a few days, contact a licensed practitioner. As with any drug, if you are pregnant or nursing a baby, seek the advice of a health care professional before taking this product.

KEEP OUT OF REACH OF CHILDREN

Keep this and all medications out of the reach of children. In case of accidental ingestion, seek professional assistance or contact a Poison Control Center immediately.

STORAGE AND HANDLING

Protect from light and heat.

Tamper Evident

Do not use this product if imprinted inner plastic shell is broken or if imprinted security strip on carton package is torn.

Made in Germany.

Distributed by:
SANUM USA Corp.
1465 Slater Road
Ferndale, WA 98248

Manufactured By:
Sanum-Kehlbeck
GmbH & Co. KG

Rev. 12/2006

PRINCIPAL DISPLAY PANEL - 10 Suppositories Carton

Pleo™ Ut
SUPPOSITORIES 6X

Homeopathic Analgesic Medicine

Indications: For temporary pain
relief of swollen lymph glands.

10 SUPPOSITORIES